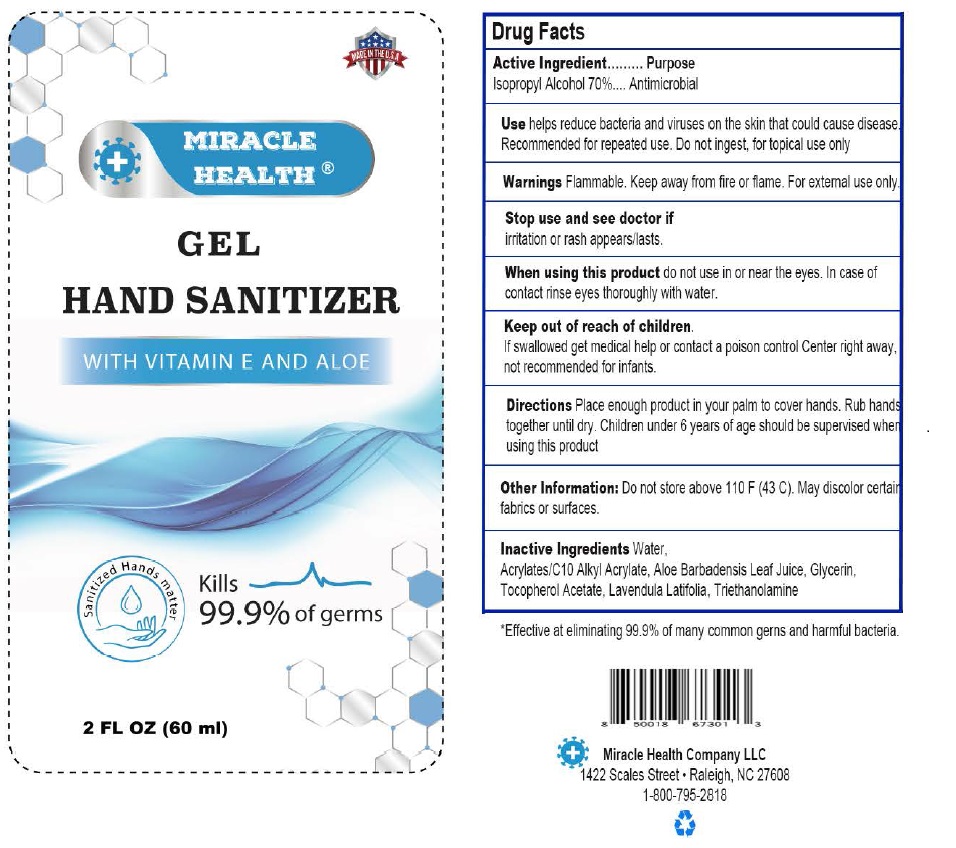 DRUG LABEL: Miracle Health Hand Sanitizer
NDC: 79668-001 | Form: GEL
Manufacturer: K W TECHNOLOGY INC
Category: otc | Type: HUMAN OTC DRUG LABEL
Date: 20200709

ACTIVE INGREDIENTS: ISOPROPYL ALCOHOL 70 mL/100 mL
INACTIVE INGREDIENTS: WATER; CARBOMER HOMOPOLYMER, UNSPECIFIED TYPE; ALOE VERA LEAF; GLYCERIN; .ALPHA.-TOCOPHEROL ACETATE; LAVANDULA LATIFOLIA WHOLE; TROLAMINE

Active Ingredient

Isopropyl Alcohol 70% v/v.

Purpose

Antimicrobial

Use

Helps reduce bacteria and viruses on the skin that could cause disease. Recommended for repeated use. Do not ingest, for topical use only.

Warnings

Flammable. Keep away from heat or flame. For external use only.

Stop use and see doctor if irritation or rash appears/lasts.
When using this product do not use in or near the eyes. In case of contact rinse eyes thoroughly with water.

Keep out of reach of children. If swallowed get medical help or contact a poison control Center right away, not recommended for infants.

Directions

- Place enough product in your palm to cover hands. Rub hand together until dry.
- Children under 6years of age should be supervised when using this product.

Other information

- Do not store above 110 F (43C).
- May discolor certain fabrics or surfaces.

Inactive ingredients

Water, Acrylates/C10 Alkyl Acrylate, Aloe Barbadensis Leaf Juice, Glycerin, Tocopherol Acetate, Lavendula Lalifolia, Triethanolamine